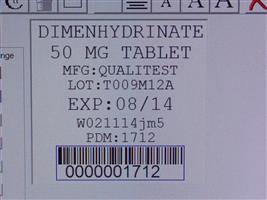 DRUG LABEL: Dimenhydrinate
NDC: 68151-1712 | Form: TABLET
Manufacturer: Carilion Materials Management
Category: otc | Type: HUMAN OTC DRUG LABEL
Date: 20121221

ACTIVE INGREDIENTS: DIMENHYDRINATE 50 mg/1 1
INACTIVE INGREDIENTS: SILICON DIOXIDE; LACTOSE MONOHYDRATE; MAGNESIUM STEARATE; CELLULOSE, MICROCRYSTALLINE; SODIUM STARCH GLYCOLATE TYPE A POTATO; STEARIC ACID

DIMENHYDRINATE TABLETS, USP 50 mg

Active ingredient (in each tablet)

Dimenhydrinate 50 mg

Purpose

Antiemetic

INDICATIONS AND USAGE

for prevention and treatment of these symptoms associated with motion sickness: Uses

- nausea
- vomiting
- dizziness

DO NOT USE

in children under 2 years of age unless directed by a doctor Do not use

Ask a doctor before use if you have

- a breathing problem such as emphysema or chronic bronchitis
- glaucoma
- difficulty in urination due to enlargement of the prostate gland

ASK DOCTOR/PHARMACIST

taking sedatives or tranquilizers Ask a doctor or pharmacist before use if you are

When using this product

- marked drowsiness may occur
- alcohol, sedatives and tranquilizers may increase drowsiness
- avoid alcoholic drinks
- be careful when driving a motor vehicle or operating machinery

PREGNANCY OR BREAST FEEDING

ask a health professional before use. If pregnant or breast-feeding,

Keep out of reach of children.

In case of overdose, get medical help or contact a Poison Control Center right away. (1-800-222-1222).

Directions

- to prevent motion sickness, the first dose should be taken 1/2 to 1 hour before starting activity
- to prevent or treat motion sickness, use the following dosing

adults and children 12 years and over | 1-2 tablets every 4-6 hours; not more than 8 tablets in 24 hours, or as directed by a doctor
children 6 years to under 12 years | 1/2-1 tablet every 6-8 hours; not more than 3 tablets in 24 hours, or as directed by a doctor
children 2 years to under 6 years | 1/4-1/2 tablet every 6-8 hours; not more than 1 1/2 tablets in 24 hours, or as directed by a doctor

Other information

store at 15° to 30°C (59° to 86°F)

You may report serious side effects to: . 130 Vintage Drive, Huntsville, AL 35811

Inactive ingredients

colloidal silicone dioxide, lactose monohydrate, magnesium stearate, microcrystalline cellulose, sodium starch glycolate, stearic acid

Made in the for Qualitest Pharmaceuticals Huntsville, AL 35811 USA

Rev. 8/09 R4 8080234 0111